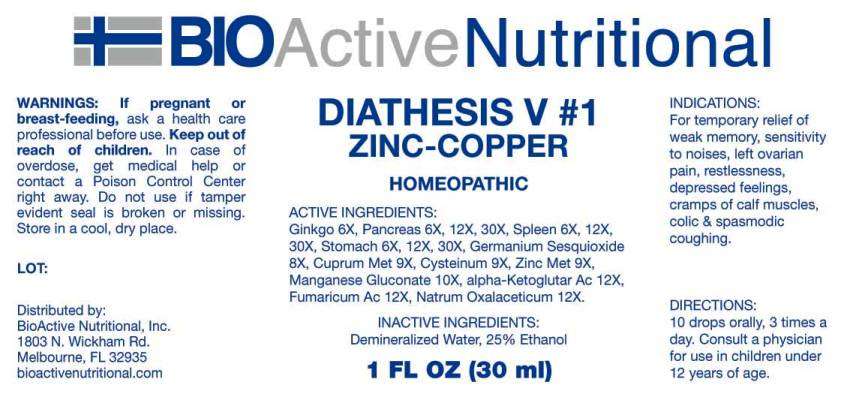 DRUG LABEL: Diathesis
NDC: 43857-0172 | Form: LIQUID
Manufacturer: BioActive Nutritional, Inc.
Category: homeopathic | Type: HUMAN OTC DRUG LABEL
Date: 20161104

ACTIVE INGREDIENTS: GINKGO 6 [hp_X]/1 mL; SUS SCROFA PANCREAS 6 [hp_X]/1 mL; SUS SCROFA SPLEEN 6 [hp_X]/1 mL; SUS SCROFA STOMACH 6 [hp_X]/1 mL; GERMANIUM SESQUIOXIDE 8 [hp_X]/1 mL; COPPER 9 [hp_X]/1 mL; CYSTEINE 9 [hp_X]/1 mL; ZINC 9 [hp_X]/1 mL; MANGANESE GLUCONATE 10 [hp_X]/1 mL; .ALPHA.-KETOGLUTARIC ACID 12 [hp_X]/1 mL; FUMARIC ACID 12 [hp_X]/1 mL; SODIUM DIETHYL OXALACETATE 12 [hp_X]/1 mL
INACTIVE INGREDIENTS: WATER; ALCOHOL

Drug Facts:

ACTIVE INGREDIENTS:

Ginkgo Biloba 6X, Pancreas (Suis) 6X, 12X, 30X, Spleen (Suis) 6X, 12X, 30X, Stomach (Suis) 6X, 12X, 30X, Germanium Sesquioxide 8X, Cuprum Metallicum 9X, Cysteinum 9X, Zincum Metallicum 9X, Manganese Gluconate 10X, Alpha-Ketoglutaricum Acidum 12X, Fumaricum Acidum 12X, Natrum Oxalaceticum 12X.

INDICATIONS:

For temporary relief of weak memory, sensitivity to noises, left ovarian pain, restlessness, depressed feelings, cramps of calf muscles, colic & spasmodic coughing.

WARNINGS:

If pregnant or breast-feeding, ask a health care professional before use.

Keep out of reach of children. In case of overdose, get medical help or contact a Poison Control Center right away.

Do not use if tamper evident seal is broken or missing.

Store in cool, dry place.

DIRECTIONS:

10 drops orally, 3 times a day. Consult a physician for use in children under 12 years of age.

INACTIVE INGREDIENTS:

Demineralized Water, 25% Ethanol.

Keep out of reach of children. In case of overdose, get medical help or contact a Poison Control Center right away.

INDICATIONS:

For temporary relief of weak memory, sensitivity to noises, left ovarian pain, restlessness, depressed feelings, cramps of calf muscles, colic & spasmodic coughing.

QUESTIONS:

Distributed by:
BioActive Nutritional, Inc.
1803 N. Wickham Rd.
Melbourne, FL 32935
bioactivenutritional.com

PACKAGE LABEL DISPLAY:

BIOActive Nutritional

DIATHESIS V 1

ZINC-COPPER

HOMEOPATHIC

1 FL OZ (30 ml)